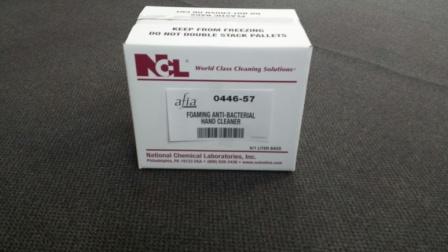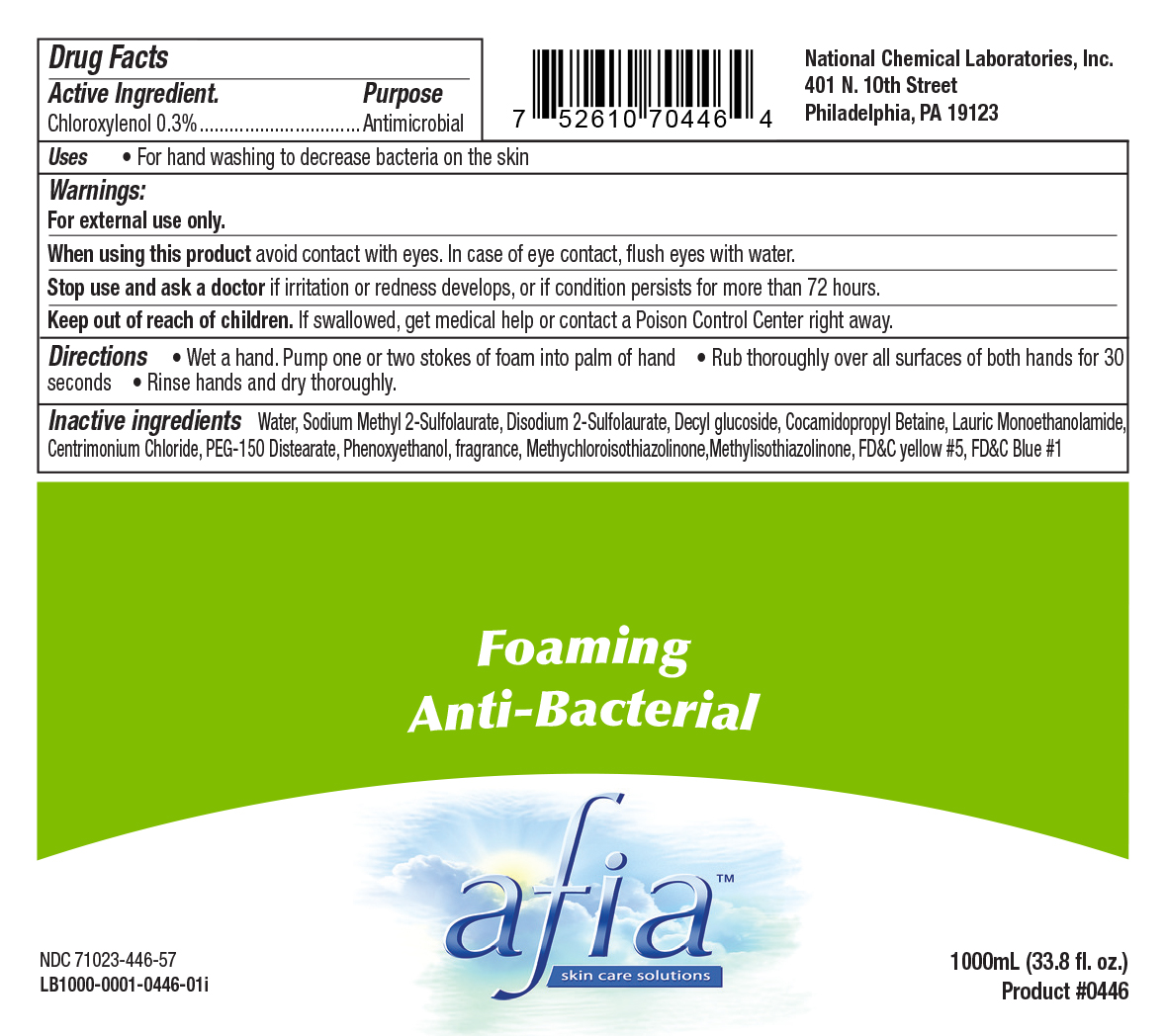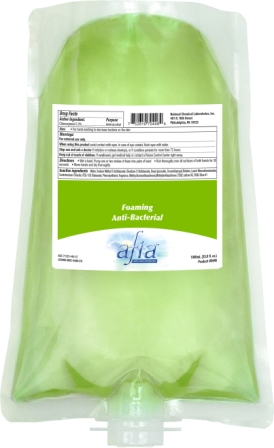 DRUG LABEL: Afia Foaming Anti-Bacterial Hand Cleaner
NDC: 71023-446 | Form: SOAP
Manufacturer: National Chemical Laboratories, Inc.
Category: otc | Type: HUMAN OTC DRUG LABEL
Date: 20221028

ACTIVE INGREDIENTS: CHLOROXYLENOL 3 mg/1 mL
INACTIVE INGREDIENTS: LAURIC MONOETHANOLAMIDE; CETRIMONIUM CHLORIDE; FD&C BLUE NO. 1; DISODIUM 2-SULFOLAURATE; DECYL GLUCOSIDE; COCAMIDOPROPYL BETAINE; WATER; PHENOXYETHANOL; SODIUM METHYL 2-SULFOLAURATE; PEG-150 DISTEARATE; METHYLCHLOROISOTHIAZOLINONE; METHYLISOTHIAZOLINONE; FD&C YELLOW NO. 5

Listing of Afia Foaming Anti-Bacterial Hand Cleaner

Drug Facts

Active Ingredient. Purpose

Chloroxylenol 0.3%............Antimicrobial

Uses

For hand washing to decrease bacteria on the skin

Warnings:

For external use only.

When using this product avoid contact with eyes. In case of eye contact, flush eyes with water.

Stop use and ask a doctor if irritation or redness develops, or if condition persists for more than 72 hours.

Directions

- Wet a hand. Pump one or two stokes of foam, into palm of hand.
- Rub thoroughly over all surfacesof both hands for 30 seconds
- Rinse hands and dry thoroughly.

Inactive ingredients

Water, Sodium Methyl 2-Sulfolaurate, Disodium 2-Sulfolaurate, Decyl glucoside, Cocamidopropyl Betaine, Lauric Monoethanolamide, Cetrimonium Chloride, PEG-150 Distearate, Phenoxyethanol, fragrance, Methylchloroisothiazolinone, Methylisothiazolinone, FD&C yellow #5, FD&C blue #1

Warnings:

Keep out of reach of children. If swallowed, get medical help or contact a Poison Control Center right away.

Uses

For hand washing to decrease bacteria on the skin